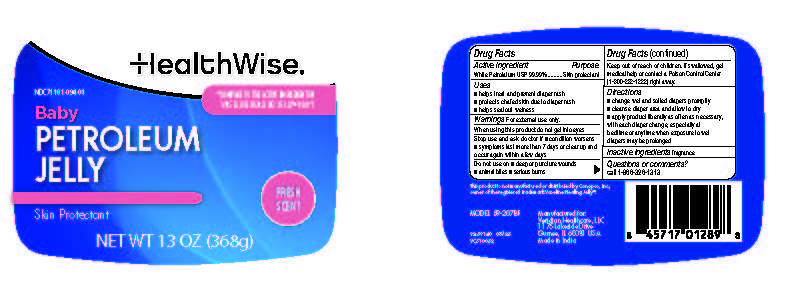 DRUG LABEL: HealthWise Petroleum Jelly Baby Fresh
NDC: 71101-094 | Form: JELLY
Manufacturer: Veridian Healthcare
Category: otc | Type: HUMAN OTC DRUG LABEL
Date: 20250925

ACTIVE INGREDIENTS: PETROLATUM 100 g/100 g
INACTIVE INGREDIENTS: WATER

HealthWise Petroleum Jelly Baby Fresh

Drug Facts

ACTIVE INGREDIENT

White Petroleum USP 99.99%

Active ingredients | Purpose
White Petrolatum 100% | Skin Protectant

Uses

■ helps treat and prevent diaper rash
■ protects chafed skin due to diaper rash
■ helps seal out wetness

Warnings

For external use only

When using this product

- do not get into eyes

Stop use and ask a doctor if

- condition worsens
- symptoms last more than 7 days or clear up and occur again within a few days

Do not use on

- deep or puncture wounds .
- animal bites
- serious burns.

Keep out of reach of children.If swallowed, get medical help or contact a Poison Control Center (1-800-222-1222) right away.

Directions

■ change wet and soiled diapers promptly
■ cleanse diaper area and allow to dry
■ apply product liberally as often as necessary, with each diaper change, especially at bedtime or anytime when exposure to wet diapers may be prolonged

Inactive ingredient

Water